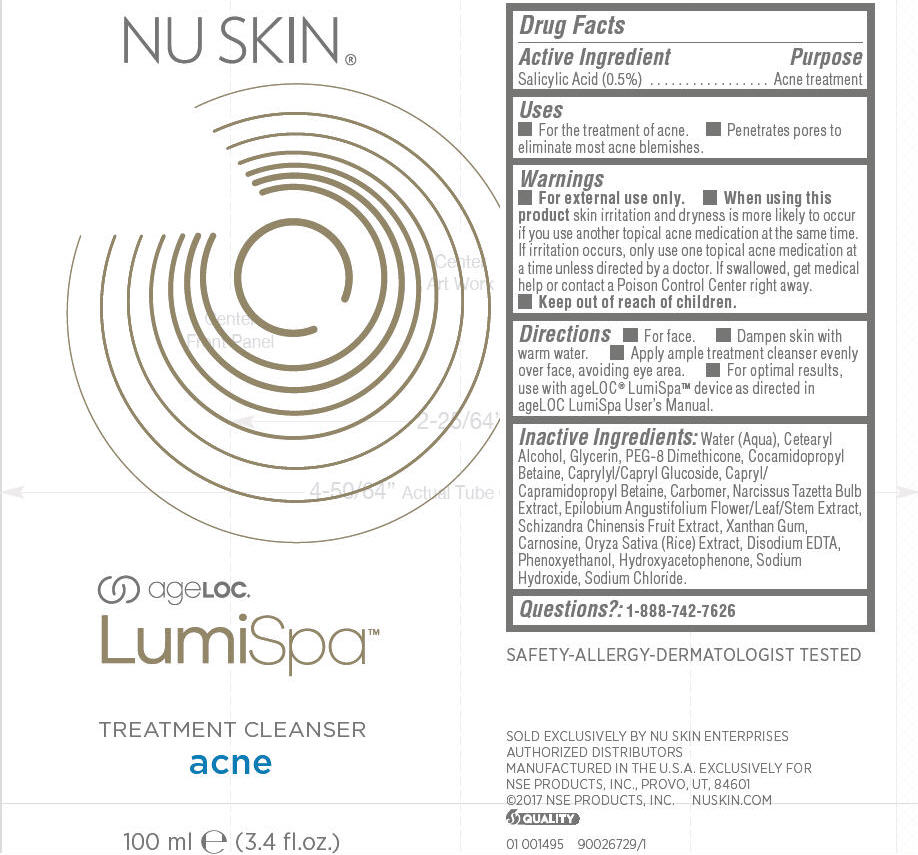 DRUG LABEL: ageLOC LumiSpa Treatment Cleanser Acne
NDC: 62839-1495 | Form: LOTION
Manufacturer: NSE Products, Inc
Category: otc | Type: HUMAN OTC DRUG LABEL
Date: 20241224

ACTIVE INGREDIENTS: Salicylic Acid 5 mg/1 mL
INACTIVE INGREDIENTS: WATER; CETOSTEARYL ALCOHOL; Glycerin; PEG-8 DIMETHICONE (600 CST); Cocamidopropyl Betaine; CAPRYLYL/CAPRYL OLIGOGLUCOSIDE; Capryl/Capramidopropyl Betaine; CARBOMER HOMOPOLYMER, UNSPECIFIED TYPE; NARCISSUS TAZETTA BULB; EPILOBIUM ANGUSTIFOLIUM FLOWERING TOP; SCHISANDRA CHINENSIS FRUIT; Xanthan Gum; Carnosine; RICE GERM; EDETATE DISODIUM ANHYDROUS; Phenoxyethanol; Sodium Hydroxide; Sodium Chloride

ageLOC® LumiSpa™ Treatment Cleanser Acne

Drug Facts

Active Ingredient

Salicylic Acid (0.5%)

Purpose

Acne treatment

Uses

- For the treatment of acne.
- Penetrates pores to eliminate most acne blemishes.

Warnings

- For external use only.

- When using this product skin irritation and dryness is more likely to occur if you use another topical acne medication at the same time. If irritation occurs, only use one topical acne medication at a time unless directed by a doctor. If swallowed, get medical help or contact a Poison Control Center right away.

- Keep out of reach of children.

Directions

- For face.
- Dampen skin with warm water.
- Apply ample treatment cleanser evenly over face, avoiding eye area.
- For optimal results, use with ageLOC® LumiSpa™ device as directed in ageLOC LumiSpa User's Manual.

Inactive Ingredients

Water (Aqua), Cetearyl Alcohol, Glycerin, PEG-8 Dimethicone, Cocamidopropyl Betaine, Caprylyl/Capryl Glucoside, Capryl/Capramidopropyl Betaine, Carbomer, Narcissus Tazetta Bulb Extract, Epilobium Angustifolium Flower/Leaf/Stem Extract, Schizandra Chinensis Fruit Extract, Xanthan Gum, Carnosine, Oryza Sativa (Rice) Extract, Disodium EDTA, Phenoxyethanol, Hydroxyacetophenone, Sodium Hydroxide, Sodium Chloride.

Questions?

1-888-742-7626

PRINCIPAL DISPLAY PANEL - 100 ml Tube Label

NU SKIN®

ageLOC®

LumiSpa™

TREATMENT CLEANSER
acne

100 ml e (3.4 fl.oz.)